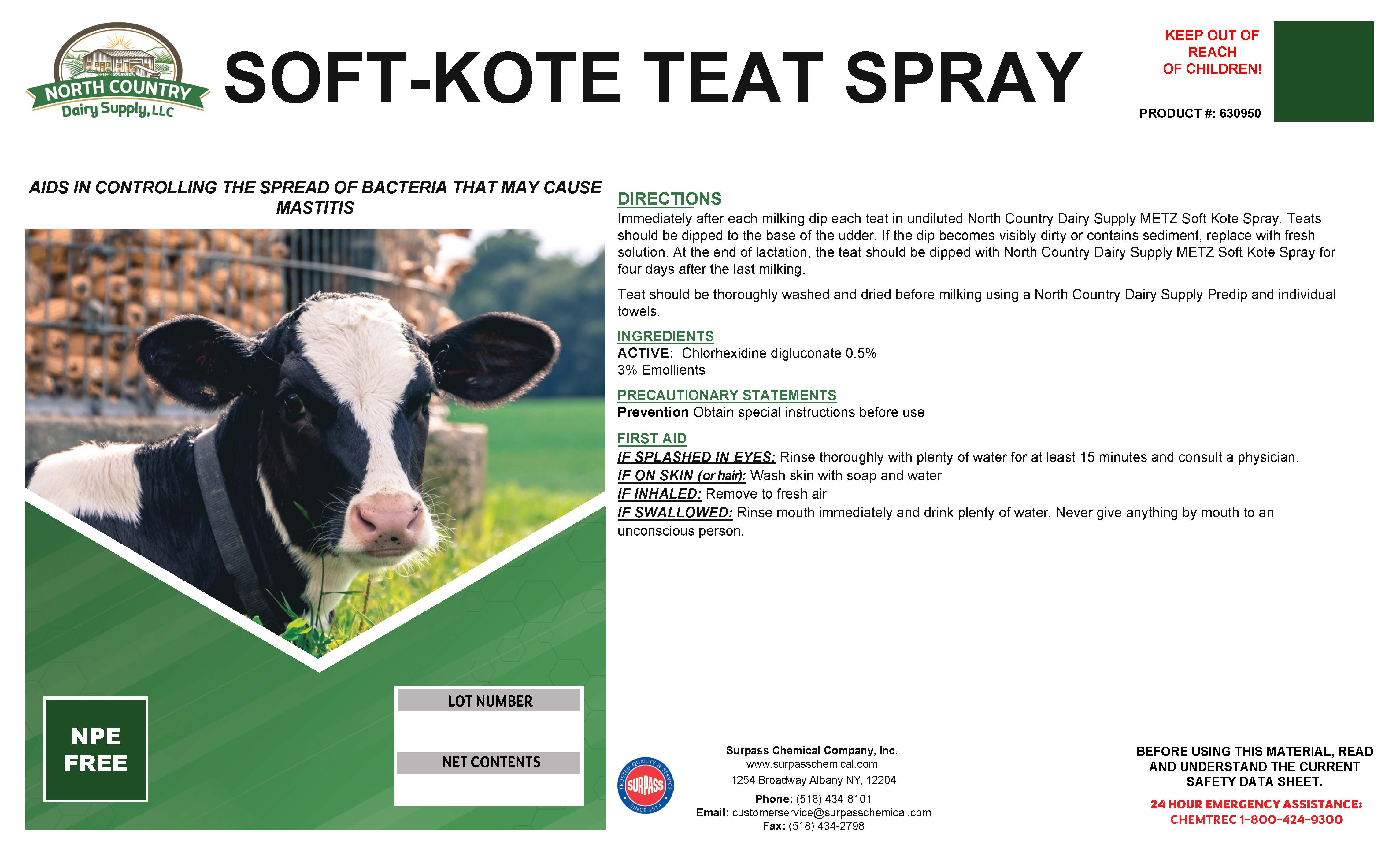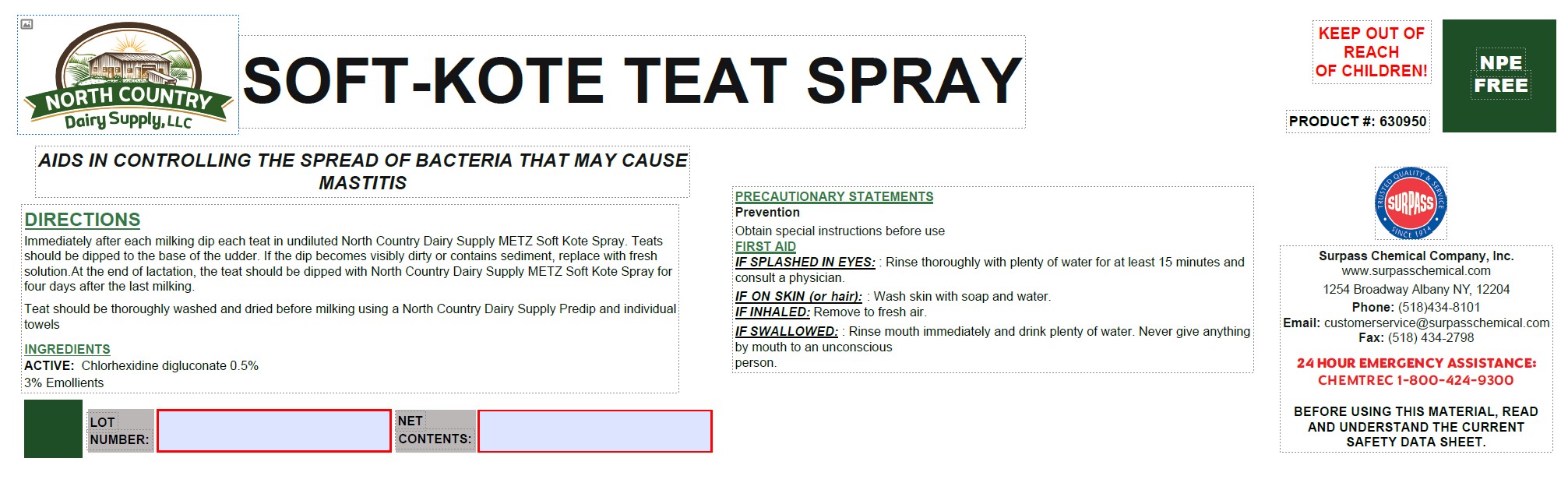 DRUG LABEL: Metz Soft Kote TeatSpray
NDC: 86067-0128 | Form: SOLUTION
Manufacturer: Surpass Chemical. Company, Inc.
Category: animal | Type: OTC ANIMAL DRUG LABEL
Date: 20240507

ACTIVE INGREDIENTS: CHLORHEXIDINE 0.005 kg/1 kg
INACTIVE INGREDIENTS: WATER 0.9547 kg/1 kg; C9-11 PARETH-8 0.01 kg/1 kg; GLYCERIN 0.03 kg/1 kg; FD&C BLUE NO. 1 0.0002 kg/1 kg; ANHYDROUS CITRIC ACID 0.0001 kg/1 kg

Metz Soft Kote Teat Spray

DESCRIPTION

SOFT KOTE TEAT SPRAY

AIDS IN CONTROLLING THE SPREAD OF BACTERIA THAT MAY CAUSE MASTITIS PRODUCT #: 630950

DIRECTIONS:

Immediately after each milking dip each teat in undiluted North Country Dairy Supply METZ Soft Kote Teat Spray. Teats should be dipped to the base of the udder. If the dip becomes visibly dirty or contains sediment, replace with fresh solution.
At the end of lactation, the teat should be dipped with North Country Dairy Supply METZ Soft Kote Teat Spray for four days after the last milking.
Teat should be thoroughly washed and dried before milking using a North Country Dairy Supply Predip and individual towels.

OTHER SAFETY INFORMATION

PRECAUTIONARY STATEMENTS
Prevention

Obtain special instructions before use.

ACTIVE INGREDIENT

INGREDIENTS:
ACTIVE: Chlorhexidine digluconate 0.5%

3% Emollients

OTHER SAFETY INFORMATION

FIRST AID:
IF SPLASHED IN EYES: Rinse thoroughly with plenty of water for at least 15 minutes and consult a physician.
IF ON SKIN (or hair): Wash skin with soap and water.
IF INHALED: Remove to fresh air.
IF SWALLOWED:Drink plenty of water. Do not induce vomiting without medical advice. Never give anything by mouth to an unconscious person. If symptons persist, call a physician.

SAFE HANDLING WARNING

BEFORE USING THIS MATERIAL, READ AND
UNDERSTAND THE CURRENT SAFETY DATA SHEET.

Surpass Chemical Company, Inc. Phone: (518) 434-8101 24 HOUR EMERGENCY ASSISTANCE:
www.surpasschemical.com Fax: (518) 434-2798 CHEMTREC 1-800-424-9300
1254 Broadway Albany NY, 12204 Email: customerservice@surpasschemical.com KEEP OUT OF REACH OF CHILDREN!

KEEP OUT OF REACH OF CHILDREN!